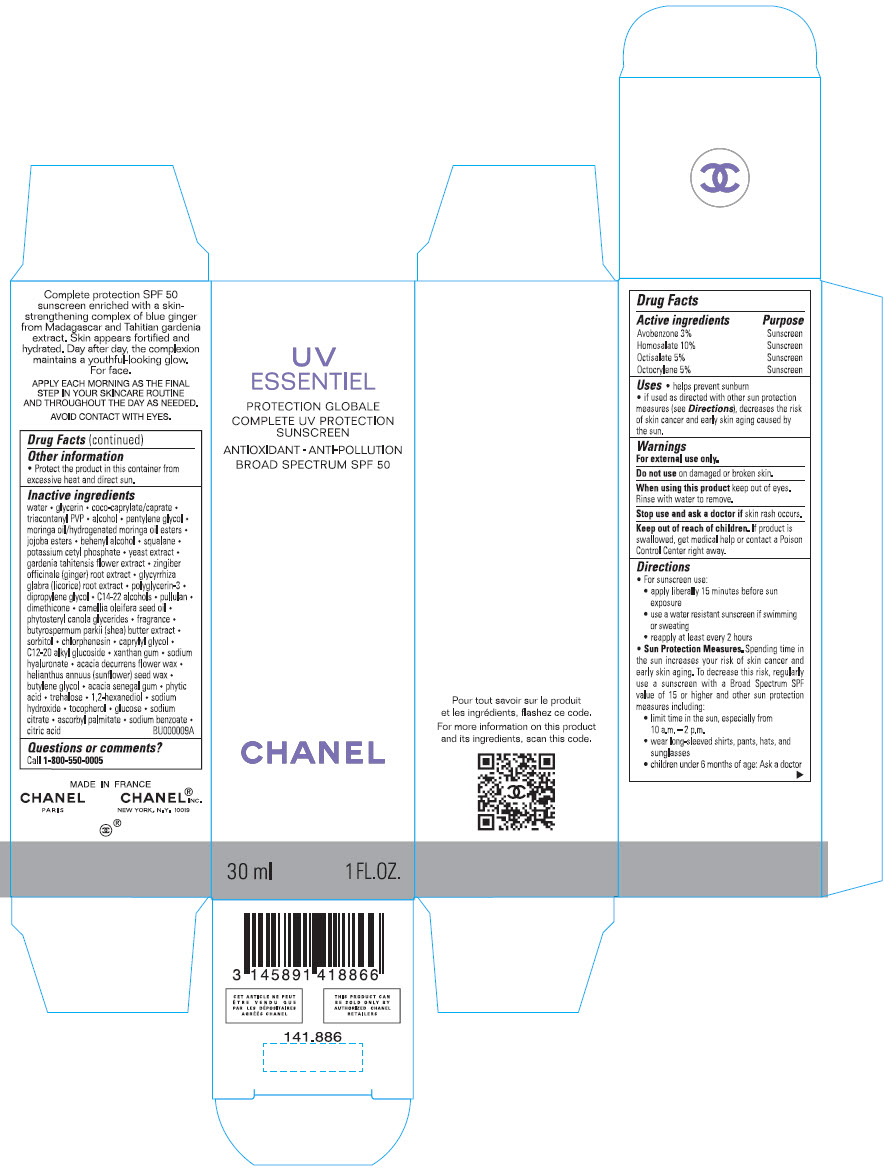 DRUG LABEL: UV ESSENTIEL 
NDC: 68745-2157 | Form: EMULSION
Manufacturer: CHANEL PARFUMS BEAUTE
Category: otc | Type: HUMAN OTC DRUG LABEL
Date: 20231208

ACTIVE INGREDIENTS: AVOBENZONE 30 mg/1 mL; HOMOSALATE 100 mg/1 mL; OCTISALATE 50 mg/1 mL; OCTOCRYLENE 50 mg/1 mL
INACTIVE INGREDIENTS: WATER; glycerin; cocoyl caprylocaprate; TRICONTANYL POVIDONE; alcohol; pentylene glycol; JOJOBA OIL, RANDOMIZED; docosanol; squalane; potassium cetyl phosphate; yeast, unspecified; GARDENIA TAITENSIS FLOWER; ginger; glycyrrhiza glabra; polyglycerin-3; dipropylene glycol; C14-22 alcohols; pullulan; dimethicone; camellia oil; shea butter; sorbitol; chlorphenesin; caprylyl glycol; C12-20 alkyl glucoside; xanthan gum; HYALURONATE SODIUM; acacia decurrens flower wax; helianthus annuus seed wax; butylene glycol; acacia; fytic acid; trehalose; 1,2-hexanediol; sodium hydroxide; tocopherol; anhydrous dextrose; sodium citrate, unspecified form; ascorbyl palmitate; sodium benzoate; anhydrous citric acid

UV ESSENTIEL
COMPLETE UV PROTECTION SUNSCREEN ANTIOXIDANT ANTI-POLLUTION BROAD SPECTRUM SPF 50

Drug Facts

ACTIVE INGREDIENT

Active ingredients | Purpose
Avobenzone 3% | Sunscreen
Homosalate 10% | Sunscreen
Octisalate 5% | Sunscreen
Octocrylene 5% | Sunscreen

Uses

- helps prevent sunburn
- if used as directed with other sun protection measures (see Directions), decreases the risk of skin cancer and early skin aging caused by the sun.

Warnings

For external use only.

Do not use on damaged or broken skin.

When using this product keep out of eyes. Rinse with water to remove.

Stop use and ask a doctor if skin rash occurs.

Keep out of reach of children. If swallowed, get medical help or contact a Poison Control Center right away.

Directions

- For sunscreen use:
  - apply liberally 15 minutes before sun exposure
  - use a water resistant sunscreen if swimming or sweating
  - reapply at least every 2 hours
- Sun Protection Measures. Spending time in the sun increases your risk of skin cancer and early skin aging. To decrease this risk, regularly use a sunscreen with a Broad Spectrum SPF value of 15 or higher and other sun protection measures including:
  - limit time in the sun, especially from 10 a.m. – 2 p.m.
  - wear long-sleeved shirts, pants, hats, and sunglasses
  - Children under 6 months of age: Ask a doctor

Other information

Protect the product in this container from excessive heat and direct sun.

Inactive ingredients

water • glycerin • coco-caprylate/caprate caprylyl • triacontanyl PVP • alcohol • pentylene glycol • moringa oil/hydrogenated moringa oil esters • jojoba esters • behenyl alcohol • squalane • potassium cetyl phosphate • yeast extract • gardenia tahitensis flower extract • zingiber officinale (ginger) root extract • glycyrrhiza glabra (licorice) root extract • polyglycerin-3 • dipropylene glycol • C14-22 alcohols • pullulan • dimethicone • camellia oleifera seed oil • phytosteryl canola glycerides • fragrance • butyrospermum parkii (shea) butter extract • sorbitol • chlorphenesin • caprylyl glycol • C12-20 alkyl glucoside • xanthan gum • sodium hyaluronate • acacia decurrens flower wax • helianthus annuus (sunflower) seed wax • butylene glycol • acacia senegal gum • phytic acid • trehalose • 1,2-hexanediol • sodium hydroxide • tocopherol • glucose • sodium citrate • ascorbyl palmitate • sodium benzoate • citric acid
BU000009A

Questions or comments?

Call 1-800-550-0005

PRINCIPAL DISPLAY PANEL - 30 ml Bottle Carton

UV
ESSENTIEL

COMPLETE UV PROTECTION
SUNSCREEN

ANTIOXIDANT - ANTI-POLLUTION
BROAD SPECTRUM SPF 50

CHANEL

30 ml
1 FL.OZ.